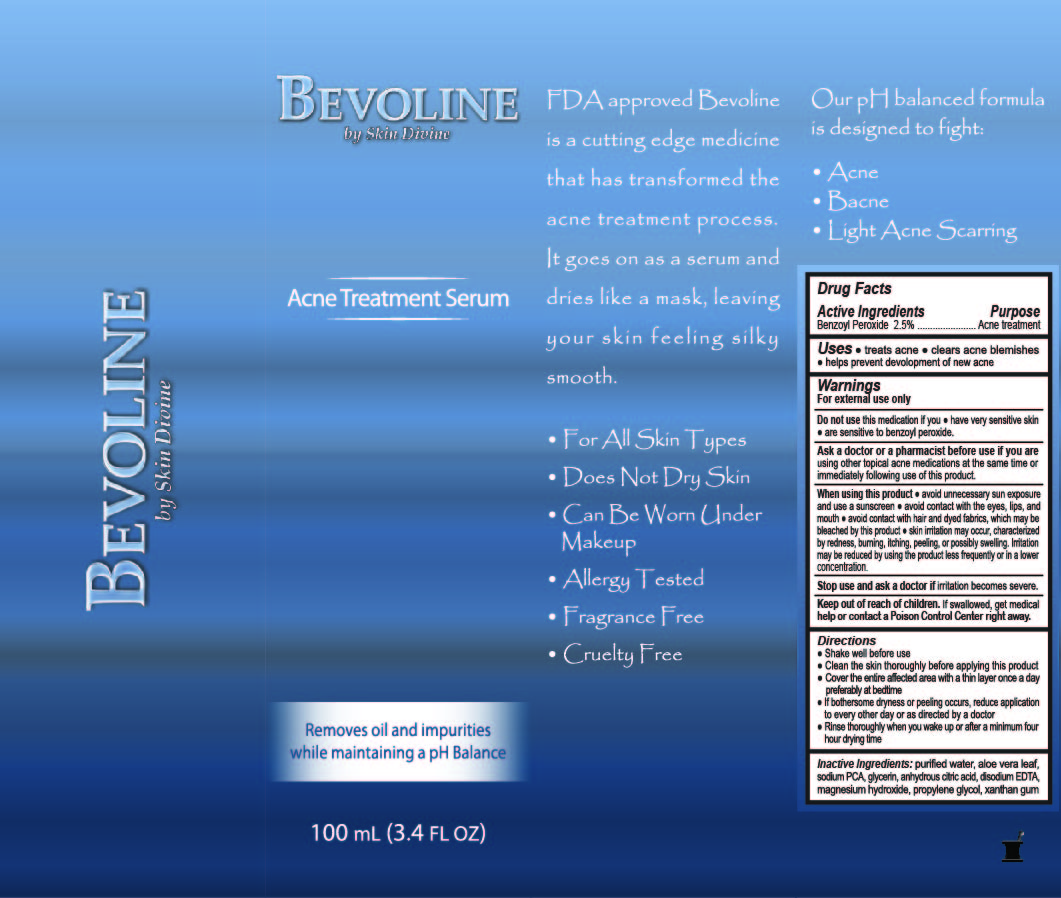 DRUG LABEL: Bevoline
NDC: 70013-302 | Form: LOTION
Manufacturer: Skin Divine Inc.
Category: otc | Type: HUMAN OTC DRUG LABEL
Date: 20160225

ACTIVE INGREDIENTS: BENZOYL PEROXIDE 2.5 g/100 mL
INACTIVE INGREDIENTS: WATER; ALOE VERA LEAF; GLYCERIN; ANHYDROUS CITRIC ACID; DISODIUM HEDTA; MAGNESIUM HYDROXIDE; XANTHAN GUM; SODIUM PYRROLIDONE CARBOXYLATE; PROPYLENE GLYCOL

STATEMENT OF IDENTITY

Bevoline
by Skin Divine

Acne Treatment Serum

Removes oil and impurities

while maintaining pH-Balance

FDA approved Bevoline is a cutting edge medicine that has transformed the acne treatment process. It goes on as a serum and dries like a mask, leaving your skin feeling silky smooth.

- For All Skin Types
- Does Not Dry Skin
- Can Be Worn Under Makeup
- Allergy Tested
- Fragrance Free
- Cruelty Free

Our pH balanced formula is designed to fight:

- Acne
- Bacne
- Light Acne Scarring

Active Ingredients
Benzoyl Peroxide 2.5%

Warnings

For external use only

Ask a doctor or a pharmacist before use if you are using other topical acne medications at the
same time or immediately following use of this product.

When using this product ● avoid unnecessary sun exposure and use a sunscreen ● avoid contact
with the eyes, lips, and mouth ● avoid contact with hair and dyed fabrics, which may be bleached
by this product ● skin irritation may occur, characterized by redness, burning, itching, peeling, or
possibly swelling. Irritation may be reduced by using the product less frequently or in a lower concentration.

Stop use and ask a doctor if irritation becomes severe.

Directions
● Shake well before use
● Clean the skin thoroughly before applying this product
● Cover the entire affected area with a thin layer once a day preferably at bedtime
● If bothersome dryness or peeling occurs, reduce application to every
other day or as directed by a doctor
● Rinse thoroughly when you wake up or after a minimum four-hour drying time

INACTIVE INGREDIENT

Inactive Ingredients purified water, aloe vera leaf, sodium PCA, glycerin, magnesium hydroxide, disodium EDTA, propylene glycol, anhydrous citric acid, xanthan gum.

Do not use this medication if you ♦ have very sensitive skin ♦ are sensitive to benzoyl peroxide.

INDICATIONS AND USAGE

Uses ♦ treats acne ♦ clears acne blemishes ♦ helps prevent development of new acne blemishes

DOSAGE AND ADMINISTRATION

Cover the entire affected area with a thin layer once a day preferably at bedtime.

PURPOSE

Acne treatment

Keep out of reach of children. If swallowed, get medical help or contact a Poison Control Center right away.